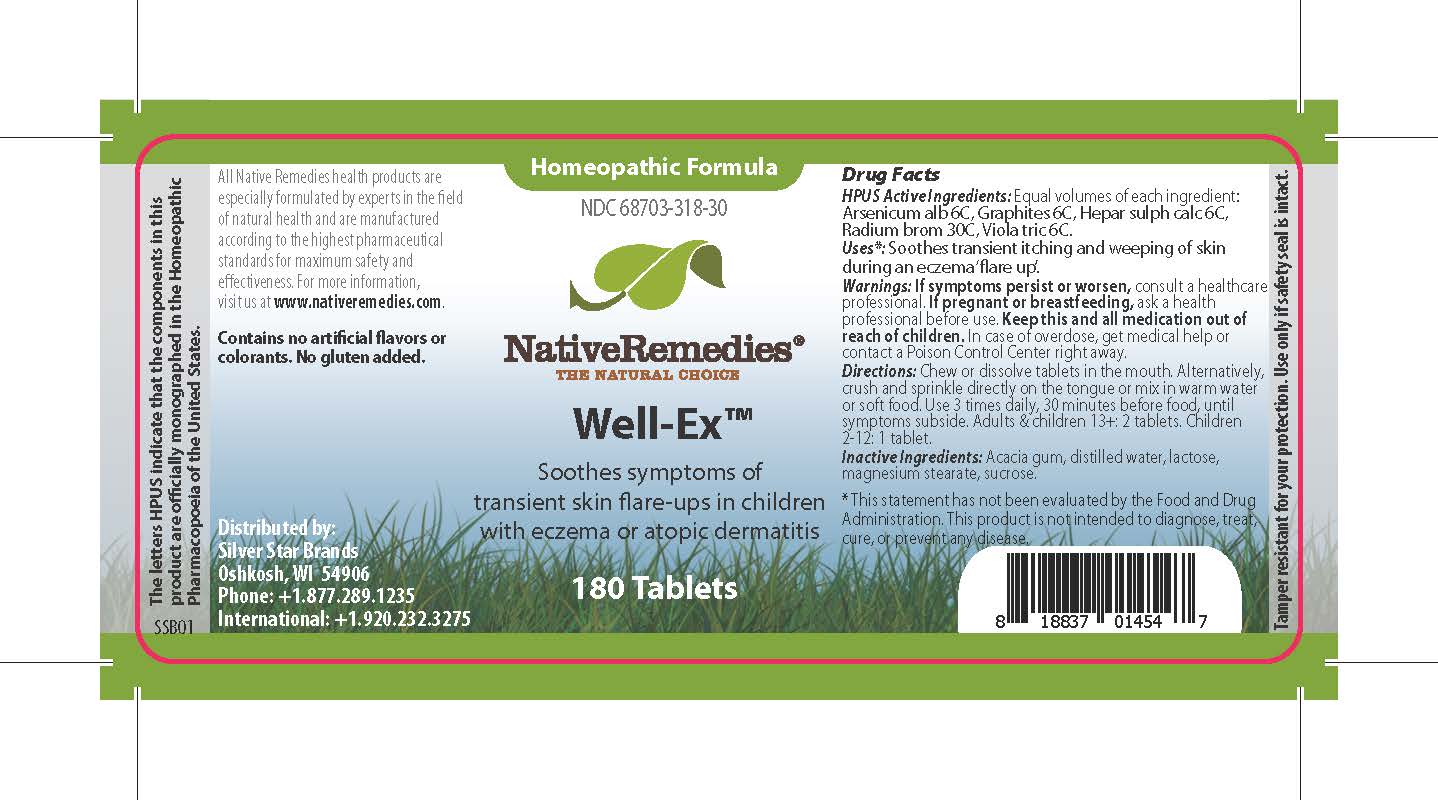 DRUG LABEL: Well-Ex
NDC: 68703-318 | Form: TABLET
Manufacturer: Silver Star Brands
Category: homeopathic | Type: HUMAN OTC DRUG LABEL
Date: 20241203

ACTIVE INGREDIENTS: GRAPHITE 6 [hp_C]/1 1; CALCIUM SULFIDE 6 [hp_C]/1 1; ARSENIC TRIOXIDE 6 [hp_C]/1 1; RADIUM BROMIDE 30 [hp_C]/1 1; VIOLA TRICOLOR 6 [hp_C]/1 1
INACTIVE INGREDIENTS: ACACIA; WATER; LACTOSE, UNSPECIFIED FORM; MAGNESIUM STEARATE; SUCROSE

NativeRemedies® Well-Ex™

HPUS Active Ingredients: Equal volumes of each ingredient: Arsenicum alb 6C, Graphites 6C, Hepar sulph calc 6C, Radium brom 30C, Viola tric 6C.

The letters HPUS indicate that the components in this product are officially monographed in the Homeopathic Pharmacopoeia of the United States.

Uses*

Uses*: Soothes transient itching and weeping of skin during an eczema 'flare up'.

*This statement has not been evaluated by the Food and Drug Administration. This product is not intended to diagnose, treat, cure, or prevent any disease.

Warnings

Warnings: If symptoms persist or worsen, consult a healthcare professional. If pregnant or breastfeeding, ask a health professional before use. Keep this and all medication out of reach of children. In case of oversdose, get medical help or contact a Poison Control Center right away.

Directions

Directions: Chew or dissolve tablets in the mouth. Alternatively, crush and sprinkle directly on the tongue or mix in warm water or soft food. Use 3 times daily, 30 minutes before food, until symptoms subside. Adults & children 13+: 2 tablets. Childeren 2-12: 1 tablet.

OTHER SAFETY INFORMATION

Contains no artificial flavors or colorants. No gluten added.

Tamper resistant for your protection. Use only if safety seal is intact.

Inactive Ingredients

Inactive Ingredients: Acacia gum, distilled water, lactose, magnesium stearate, sucrose.

KEEP OUT OF REACH OF CHILDREN

Keep this and all medication out of reach of children.

PREGNANCY OR BREAST FEEDING

If pregnant or breastfeeding, ask a health professional before use.

PURPOSE

Soothes symptoms of transient skin flare-ups in children with eczema or atopic dermatitis.